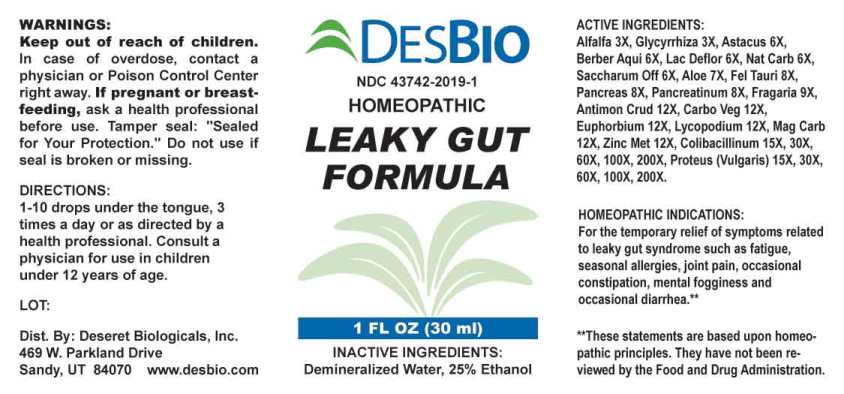 DRUG LABEL: Leaky Gut Formula
NDC: 43742-2019 | Form: LIQUID
Manufacturer: Deseret Biologicals, Inc.
Category: homeopathic | Type: HUMAN OTC DRUG LABEL
Date: 20230714

ACTIVE INGREDIENTS: MEDICAGO SATIVA WHOLE 3 [hp_X]/1 mL; GLYCYRRHIZA GLABRA 3 [hp_X]/1 mL; ASTACUS ASTACUS 6 [hp_X]/1 mL; BERBERIS AQUIFOLIUM ROOT BARK 6 [hp_X]/1 mL; SKIM MILK 6 [hp_X]/1 mL; SODIUM CARBONATE 6 [hp_X]/1 mL; SUCROSE 6 [hp_X]/1 mL; ALOE 7 [hp_X]/1 mL; BOS TAURUS BILE 8 [hp_X]/1 mL; SUS SCROFA PANCREAS 8 [hp_X]/1 mL; PANCRELIPASE 8 [hp_X]/1 mL; FRAGARIA VESCA FRUIT 9 [hp_X]/1 mL; ANTIMONY TRISULFIDE 12 [hp_X]/1 mL; ACTIVATED CHARCOAL 12 [hp_X]/1 mL; EUPHORBIA RESINIFERA RESIN 12 [hp_X]/1 mL; LYCOPODIUM CLAVATUM SPORE 12 [hp_X]/1 mL; MAGNESIUM CARBONATE 12 [hp_X]/1 mL; ZINC 12 [hp_X]/1 mL; ESCHERICHIA COLI 15 [hp_X]/1 mL; PROTEUS VULGARIS 15 [hp_X]/1 mL
INACTIVE INGREDIENTS: WATER; ALCOHOL

DRUG FACTS:

ACTIVE INGREDIENTS:

Alfalfa 3X, Glycyrrhiza Glabra 3X, Astacus Fluviatilis 6X, Berberis Aquifolium 6X, Lac Defloratum 6X, Natrum Carbonicum 6X, Saccharum Officinale 6X, Aloe 7X, Fel Tauri 8X, Pancreas Suis 8X, Pancreatinum 8X, Fragaria Vesca 9X, Antimonium Crudum 12X, Carbo Vegetabilis 12X, Euphorbium Officinarum 12X, Lycopodium Clavatum 12X, Magnesia Carbonica 12X, Zincum Metallicum 12X, Colibacillinum Cum Natrum Muriaticum 15X, 30X, 60X, 100X, 200X, Proteus (Vulgaris) 15X, 30X, 60X, 100X, 200X.

HOMEOPATHIC INDICATIONS:

For the temporary relief of symptoms related to leaky gut syndrome such as fatigue, seasonal allergies, joint pain, occasional constipation, mental fogginess and occasional diarrhea.**

**These statements are based upon homeopathic principles. They have not been reviewed by the Food and Drug Administration.

WARNINGS:

Keep out of reach of children. In case of overdose, contact a physician or Poison Control Center right away.

If pregnant or breast-feeding, ask a health professional before use.

Tamper seal: "Sealed for Your Protection." Do not use if seal is broken or missing.

Keep out of reach of children. In case of overdose, contact a physician or Poison Control Center right away.

DIRECTIONS:

1-10 drops under the tongue, 3 times a day or as directed by a health professional. Consult a physician for use in children under 12 years of age.

HOMEOPATHIC INDICATIONS:

For the temporary relief of symptoms related to leaky gut syndrome such as fatigue, seasonal allergies, joint pain, occasional constipation, mental fogginess and occasional diarrhea.**

**These statements are based upon homeopathic principles. They have not been reviewed by the Food and Drug Administration.

INACTIVE INGREDIENTS:

Demineralized Water, 25% Ethanol

QUESTIONS:

Dist. By: Deseret Biologicals, Inc.

469 W. Parkland Drive

Sandy, UT 84070 www.desbio.com

PACKAGE LABEL DISPLAY:

DESBIO

NDC 43742-2019-1

HOMEOPATHIC

LEAKY GUT

FORMULA

1 FL OZ (30 ml)